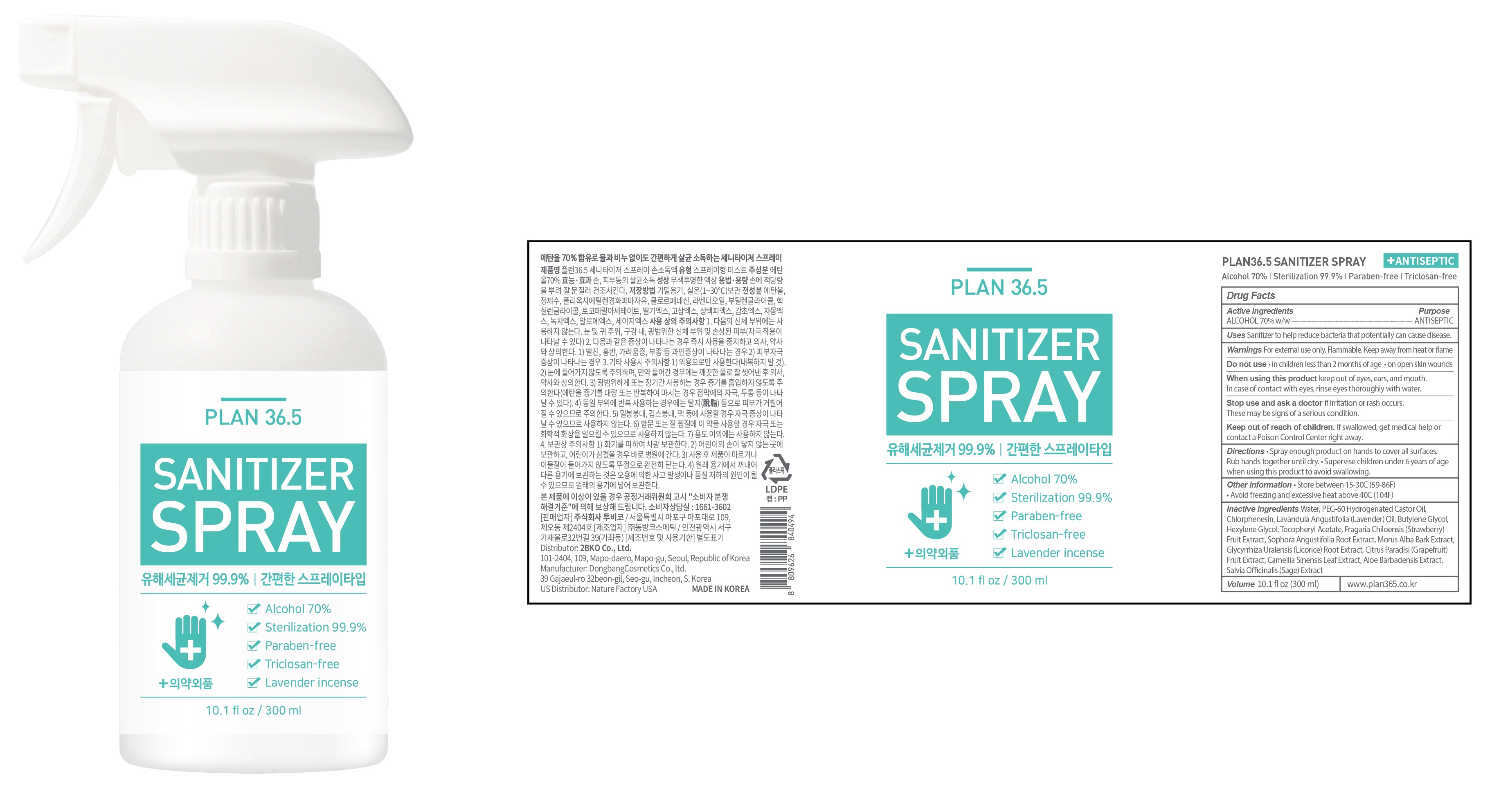 DRUG LABEL: PLAN 36.5 SANITIZER
NDC: 73264-013 | Form: SPRAY
Manufacturer: 2bko
Category: otc | Type: HUMAN OTC DRUG LABEL
Date: 20200601

ACTIVE INGREDIENTS: ALCOHOL 210 mL/300 mL
INACTIVE INGREDIENTS: Water; PEG-60 Hydrogenated Castor Oil; Chlorphenesin; LAVENDER OIL; Butylene Glycol; Hexylene Glycol; .ALPHA.-TOCOPHEROL ACETATE; BEACH STRAWBERRY; SOPHORA FLAVESCENS ROOT; MORUS ALBA BARK; GLYCYRRHIZA URALENSIS ROOT; GRAPEFRUIT; GREEN TEA LEAF; ALOE VERA LEAF; SALVIA OFFICINALIS ROOT

ACTIVE INGREDIENT

ALCOHOL 70% w/w

INACTIVE INGREDIENTS

Water, PEG-60 Hydrogenated Castor Oil, Chlorphenesin, Lavandula Angustifolia (Lavender) Oil, Butylene Glycol, Hexylene Glycol, Tocopheryl Acetate, Fragaria Chiloensis (Strawberry) Fruit Extract, Sophora Angustifolia Root Extract, Morus Alba Bark Extract, Glycyrrhiza Uralensis (Licorice) Root Extract, Citrus Paradisi (Grapefruit) Fruit Extract, Camellia Sinensis Leaf Extract, Aloe Barbadensis Extract, Salvia Officinalis (Sage) Extract

PURPOSE

ANTISEPTIC

WARNINGS

For external use only. Flammable. Keep away from heat or flame

--------------------------------------------------------------------------------------------------------
Do not use
• in children less than 2 months of age
• on open skin wounds
--------------------------------------------------------------------------------------------------------
When using this product keep out of eyes, ears, and mouth. In case of contact with eyes, rinse eyes thoroughly with water.
--------------------------------------------------------------------------------------------------------
Stop use and ask a doctor if irritation or rash occurs. These may be signs of a serious condition.

KEEP OUT OF REACH OF CHILDREN

If swallowed, get medical help or contact a Poison Control Center right away.

Uses

Sanitizer to help reduce bacteria that potentially can cause disease.

Directions

• Spray enough product on hands to cover all surfaces. Rub hands together until dry.
• Supervise children under 6 years of age when using this product to avoid swallowing.

Other information

• Store between 15-30C (59-86F)

• Avoid freezing and excessive heat above 40C (104F)